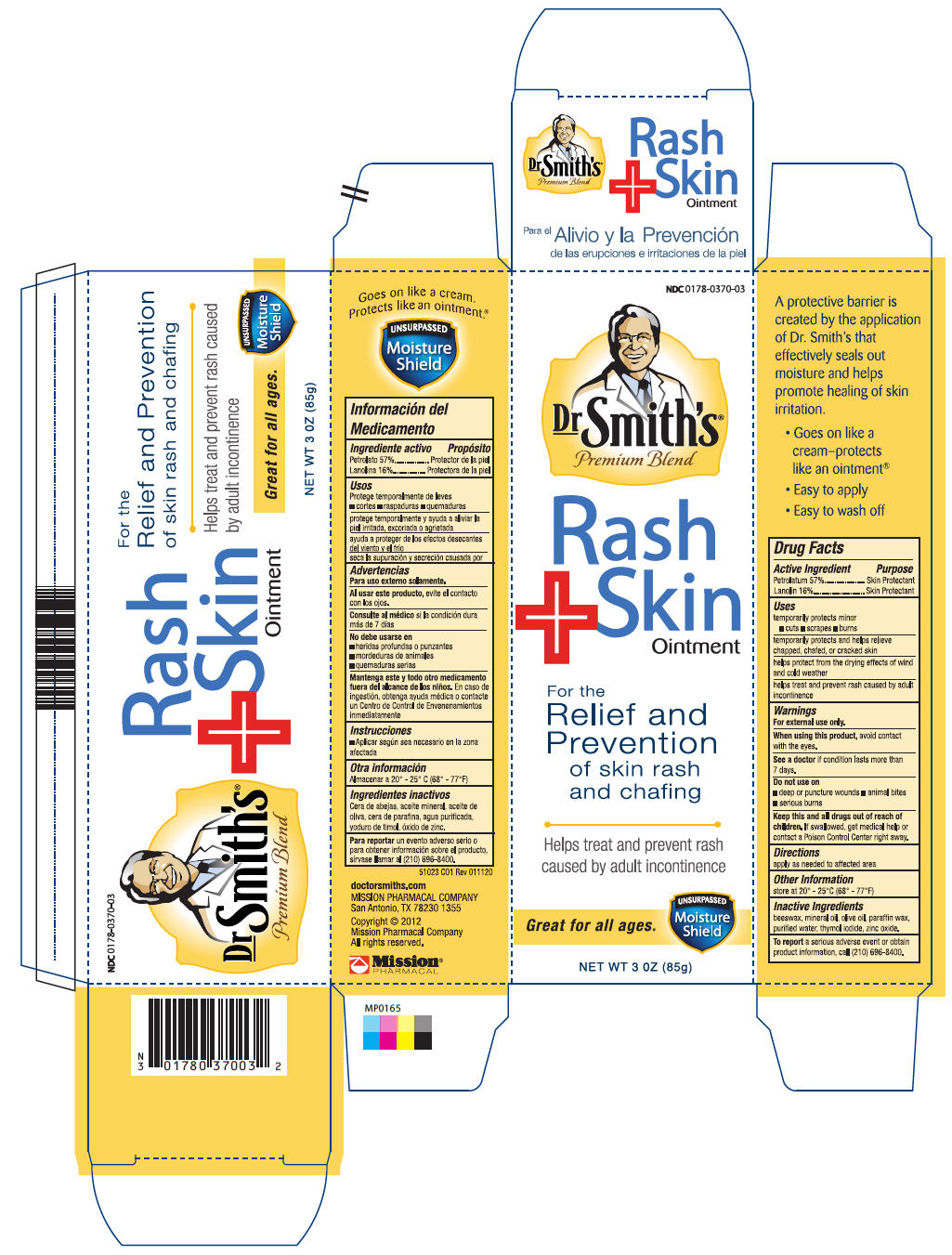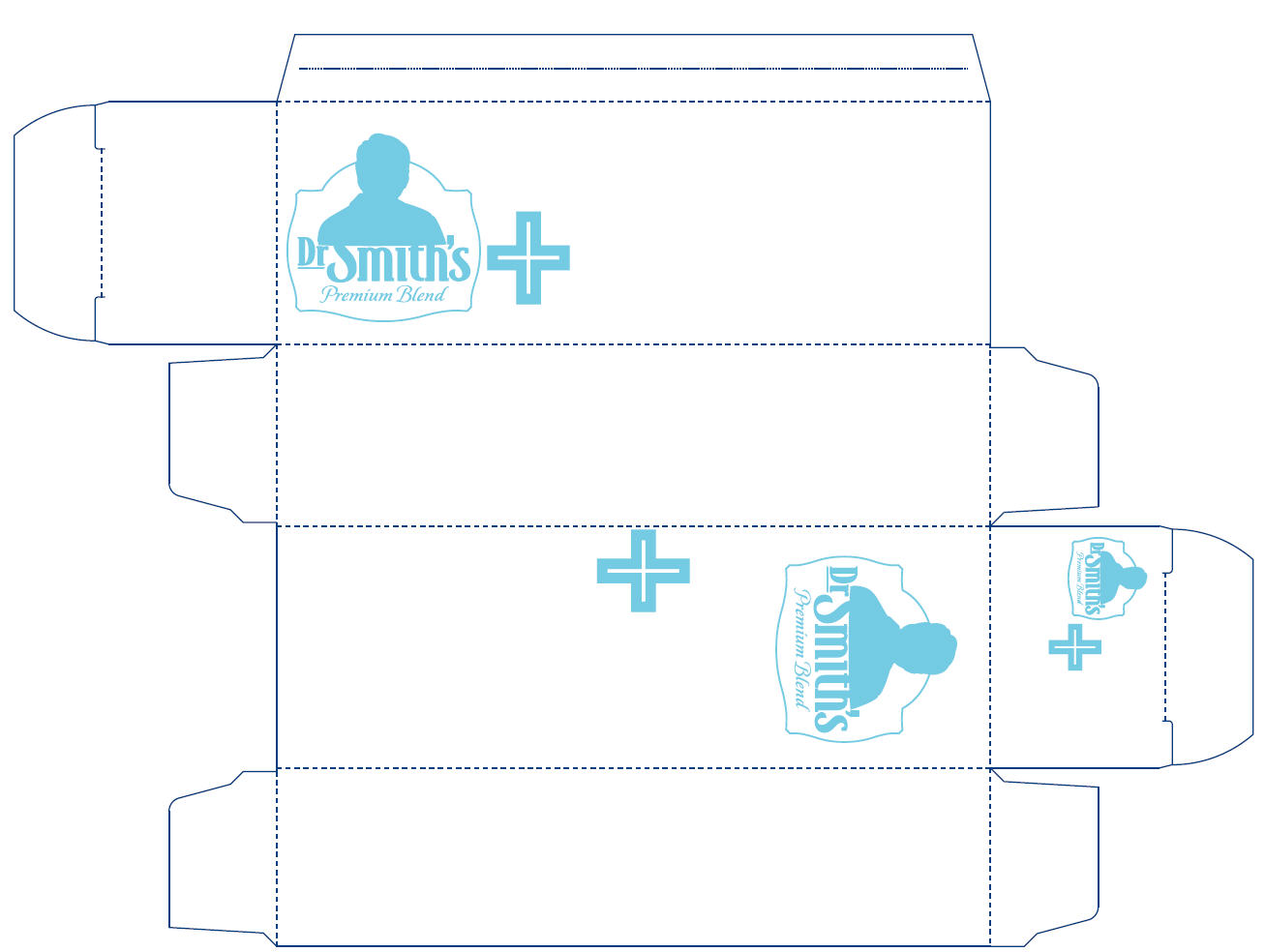 DRUG LABEL: Dr. Smiths Rash and Skin
NDC: 0178-0370 | Form: OINTMENT
Manufacturer: Mission Pharmacal Company
Category: otc | Type: HUMAN OTC DRUG LABEL
Date: 20130403

ACTIVE INGREDIENTS: ZINC OXIDE 10 g/100 g
INACTIVE INGREDIENTS: PETROLATUM 57.18 g/100 g; LANOLIN 16.05 g/100 g; ZINC OXIDE 10 g/100 g; MINERAL OIL 6.60 g/100 g; WATER 4.60 g/100 g; WHITE WAX 2.07 g/100 g; OLIVE OIL 2 g/100 g; THYMOL IODIDE 1 g/100 g; PARAFFIN .5 g/100 g

Dr. Smith's® Rash+Skin

Drug Facts

Active Ingredient | Purpose
Petrolatum 57% | Skin Protectant
Lanolin 16% | Skin Protectant

Uses

temporarily protest minor:

- cuts
- scrapes
- burns

INDICATIONS AND USAGE

Temporarily protects and helps relieve chapped, chafed, or cracked skin.

Helps protect from the dying effects of wind and cold weather.

Helps treat and prevent rash caused by adult incontinence.

Warnings

For external use only.

When using this product, avoid contact with eyes.

ASK DOCTOR

See a doctor if condition lasts more than 7 days.

Do not use on
- deep or puncture wounds
- animal bites
- serious burns

KEEP OUT OF REACH OF CHILDREN

Keep this and all drugs out of the reach of children. If swallowed, get medical help or contact a Poison Control Center right away.

Directions

Apply as needed to affected area.

Other Information

Store at 20° – 25°C (68° – 77° F)

INACTIVE INGREDIENT

beeswax, mineral oil, olive oil, paraffin wax, purified water, thymol iodide, zinc oxide.

STOP USE

To report a serious adverse event or obtain product information, call (210) 696-8400

MISSION PHARMACAL COMPANY
San Antonio, TX 78230-1355

51023
Rev 011120

PACKAGE LABEL

Dr Smith’s Rash+Skin Ointment Carton
NDC: 0178-0370-03